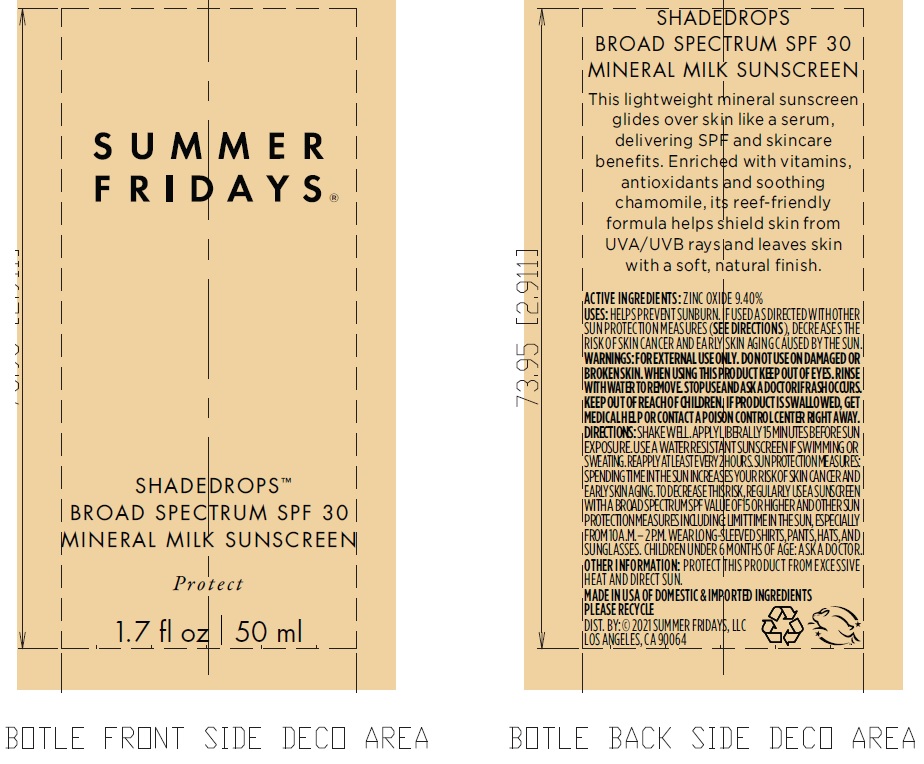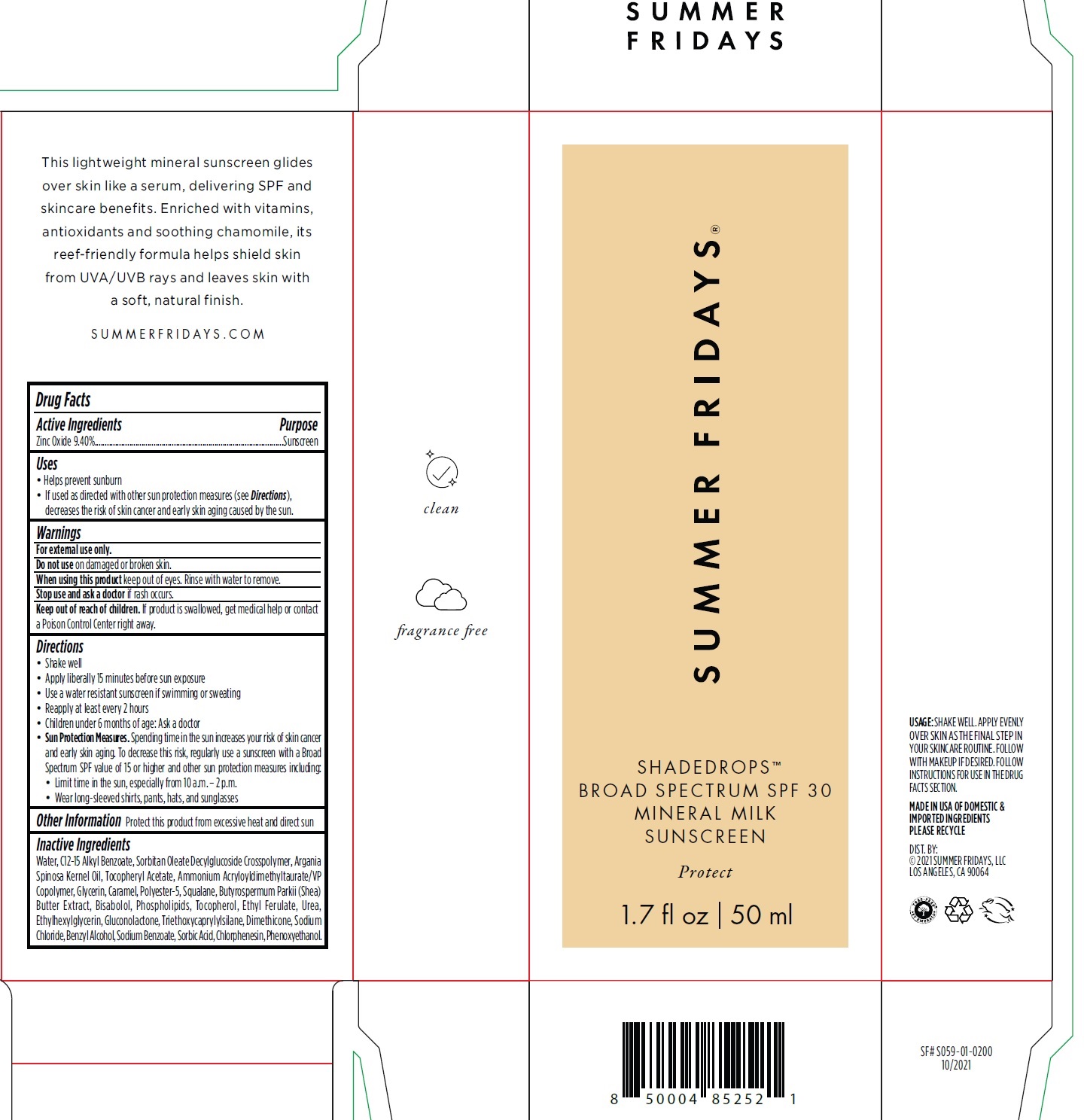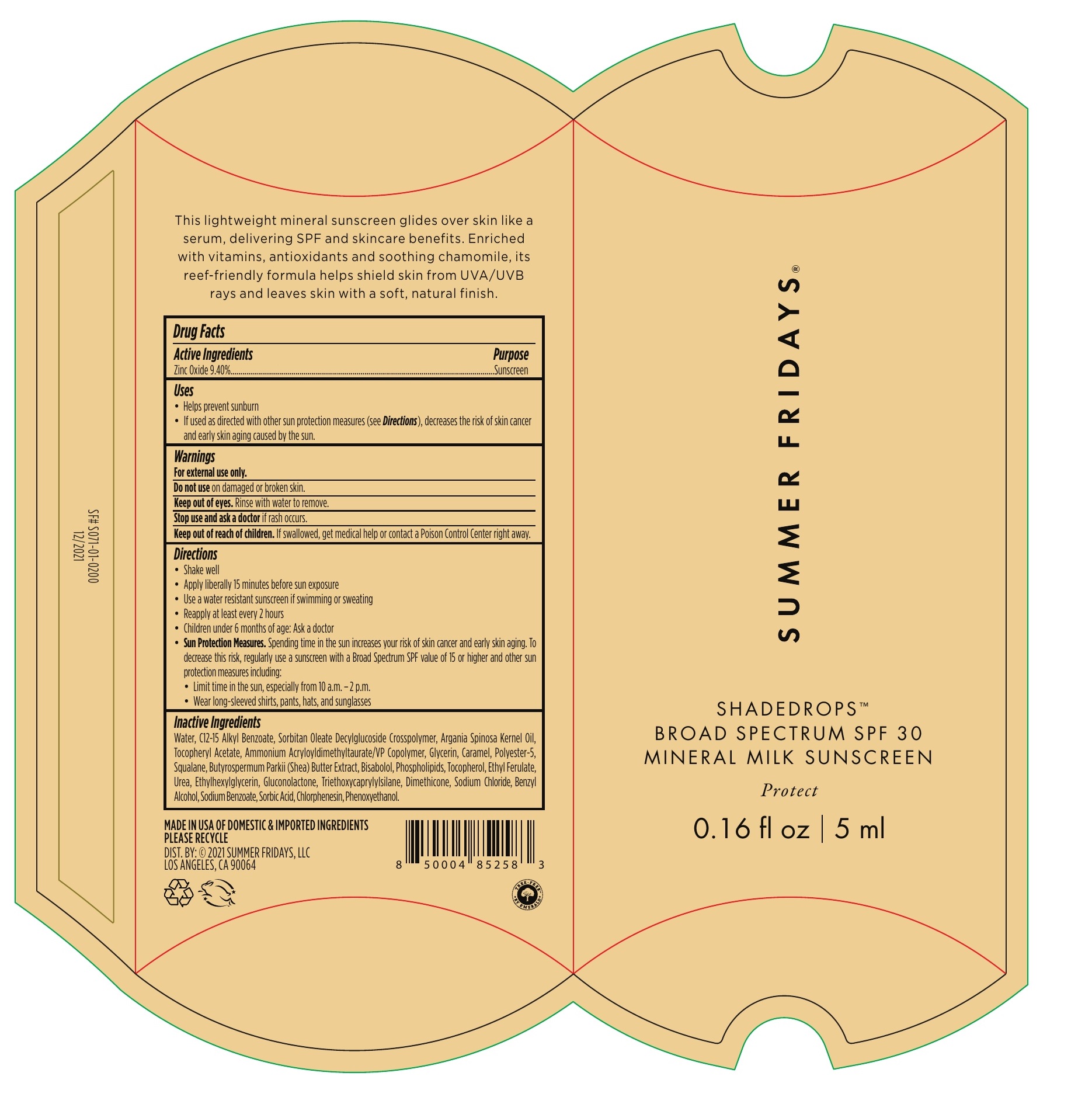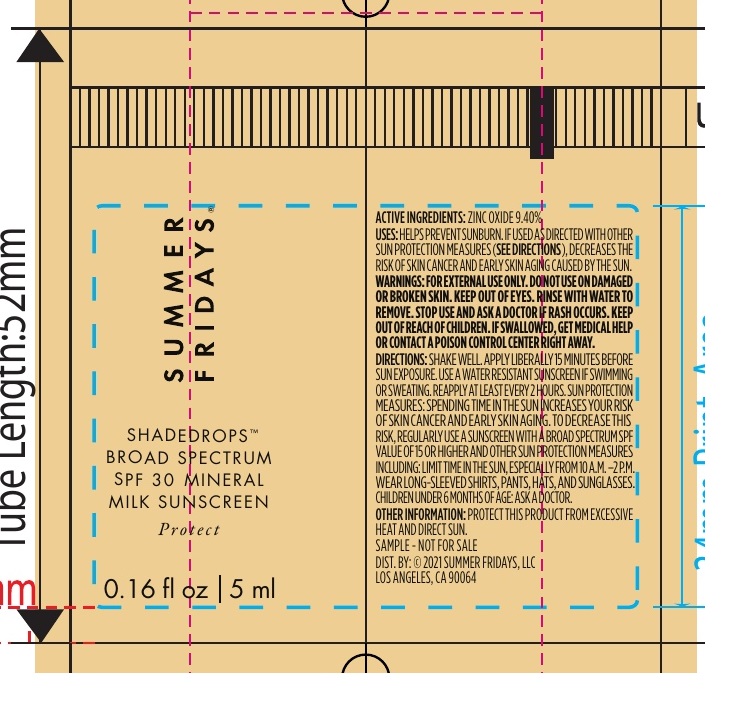 DRUG LABEL: Summer Fridays Shadedrops Broad Spectrum SPF 30 Mineral Milk Sunscreen
NDC: 81678-000 | Form: CREAM
Manufacturer: Summer Fridays LLC
Category: otc | Type: HUMAN OTC DRUG LABEL
Date: 20231026

ACTIVE INGREDIENTS: ZINC OXIDE 94 mg/1 mL
INACTIVE INGREDIENTS: POLYESTER-5 (TG-38); WATER; ALKYL (C12-15) BENZOATE; ARGAN OIL; .ALPHA.-TOCOPHEROL ACETATE; AMMONIUM ACRYLOYLDIMETHYLTAURATE/VP COPOLYMER; GLYCERIN; CARAMEL; SQUALANE; SHEA BUTTER; LEVOMENOL; TOCOPHEROL; ETHYL FERULATE; UREA; ETHYLHEXYLGLYCERIN; GLUCONOLACTONE; TRIETHOXYCAPRYLYLSILANE; DIMETHICONE; SODIUM CHLORIDE; BENZYL ALCOHOL; SODIUM BENZOATE; SORBIC ACID; CHLORPHENESIN; PHENOXYETHANOL

Summer Fridays Shadedrops Broad Spectrum SPF 30 Mineral Milk Sunscreen

Active Ingredients

Zinc Oxide 9.40%

Purpose

Sunscreen

Uses

• Helps prevent sunburn • If used as directed with other sun protection measures (see Directions), decreases the risk of skin cancer and early skin aging caused by the sun.

Warnings

For external use only.

Do not use

on damaged or broken skin.

When using this product

keep out of eyes. Rinse with water to remove.

Stop use and ask a doctor

if rash occurs.

Keep out of reach of children.

If product is swallowed, get medical help or contact a Poison Control Center right away.

Directions

• Shake well • Apply liberally 15 minutes before sun exposure • Use a water resistant sunscreen if swimming or sweating • Reapply at least every 2 hours • Children under 6 months of age: Ask a doctor • Spending time in the sun increases your risk of skin cancer and early skin aging. To decrease this risk, regularly use a sunscreen with a Broad Spectrum SPF value of 15 or higher and other sun protection measures including: • Limit time in the sun, especially from 10 a.m. – 2 p.m. • Wear long-sleeved shirts, pants, hats, and sunglasses
Sun Protection Measures.

Other Information

Protect this product from excessive heat and direct sun

Inactive Ingredients

Water, C12-15 Alkyl Benzoate, Sorbitan Oleate Decylglucoside Crosspolymer, Argania Spinosa Kernel Oil, Tocopheryl Acetate, Ammonium Acryloyldimethyltaurate/VP Copolymer, Glycerin, Caramel, Polyester-5, Squalane, Butyrospermum Parkii (Shea) Butter Extract, Bisabolol, Phospholipids, Tocopherol, Ethyl Ferulate, Urea, Ethylhexylglycerin, Gluconolactone, Triethoxycaprylylsilane, Dimethicone, Sodium Chloride, Benzyl Alcohol, Sodium Benzoate, Sorbic Acid, Chlorphenesin, Phenoxyethanol.